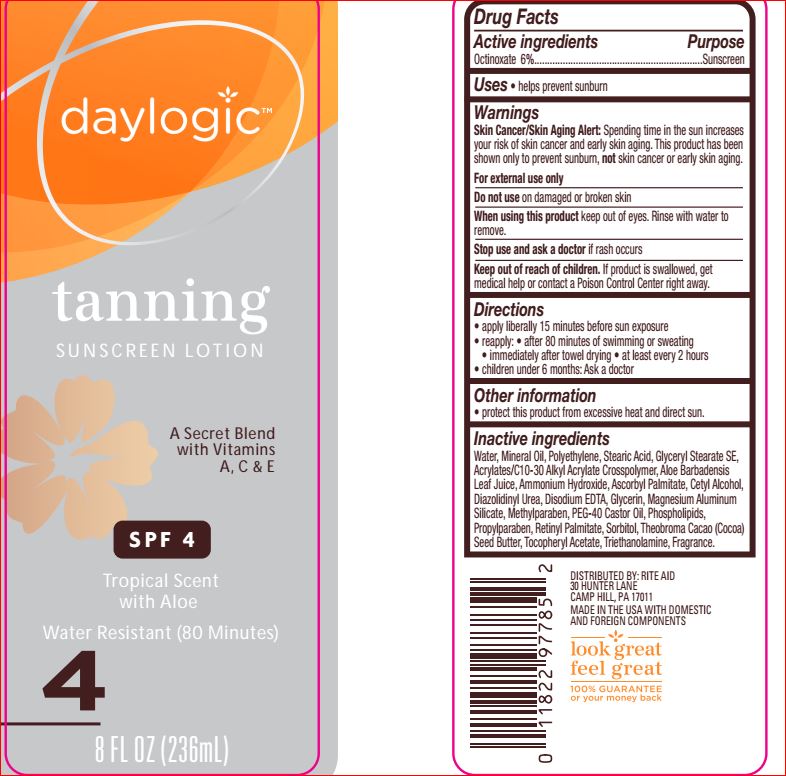 DRUG LABEL: Tanning Sunscreen SPF 4
NDC: 11822-7788 | Form: LOTION
Manufacturer: Rite Aid
Category: otc | Type: HUMAN OTC DRUG LABEL
Date: 20180515

ACTIVE INGREDIENTS: Octinoxate 6 g/100 mL
INACTIVE INGREDIENTS: CARBOMER INTERPOLYMER TYPE A (ALLYL SUCROSE CROSSLINKED); ALOE VERA LEAF; AMMONIA; Ascorbyl Palmitate; Cetyl Alcohol; Diazolidinyl Urea; EDETATE DISODIUM; Glycerin; Glyceryl Stearate SE; Magnesium Aluminum Silicate; Methylparaben; Mineral Oil; PEG-40 Castor Oil; LECITHIN, SOYBEAN; HIGH DENSITY POLYETHYLENE; Propylparaben; VITAMIN A PALMITATE; Sorbitol; Stearic Acid; COCOA BUTTER; .ALPHA.-TOCOPHEROL ACETATE; TROLAMINE; WATER

Drug Facts

Active ingredients Purpose
Octinoxate 6%.................................................................Sunscreen

INDICATIONS AND USAGE

Uses • helps prevent sunburn

Warnings
Skin Cancer/Skin Aging Alert: Spending time in the sun increases
your risk of skin cancer and early skin aging. This product has been
shown only to prevent sunburn, not skin cancer or early skin aging.
For external use only

Do not use on damaged or broken skin
When using this product keep out of eyes. Rinse with water to
remove.
Stop use and ask a doctor if rash occurs

Keep out of reach of children. If product is swallowed, get medical help or contact a Poison Control Center right away.

Directions
• apply liberally 15 minutes before sun exposure
• reapply: • after 80 minutes of swimming or sweating
• immediately after towel drying • at least every 2 hours
• children under 6 months: Ask a doctor

Other information
• protect this product from excessive heat and direct sun.

Inactive ingredients
Water, Mineral Oil, Polyethylene, Stearic Acid, Glyceryl Stearate SE,
Acrylates/C10-30 Alkyl Acrylate Crosspolymer, Aloe Barbadensis
Leaf Juice, Ammonium Hydroxide, Ascorbyl Palmitate, Cetyl Alcohol,
Diazolidinyl Urea, Disodium EDTA, Glycerin, Magnesium Aluminum
Silicate, Methylparaben, PEG-40 Castor Oil, Phospholipids,
Propylparaben, Retinyl Palmitate, Sorbitol, Theobroma Cacao (Cocoa)
Seed Butter, Tocopheryl Acetate, Triethanolamine, Fragrance.